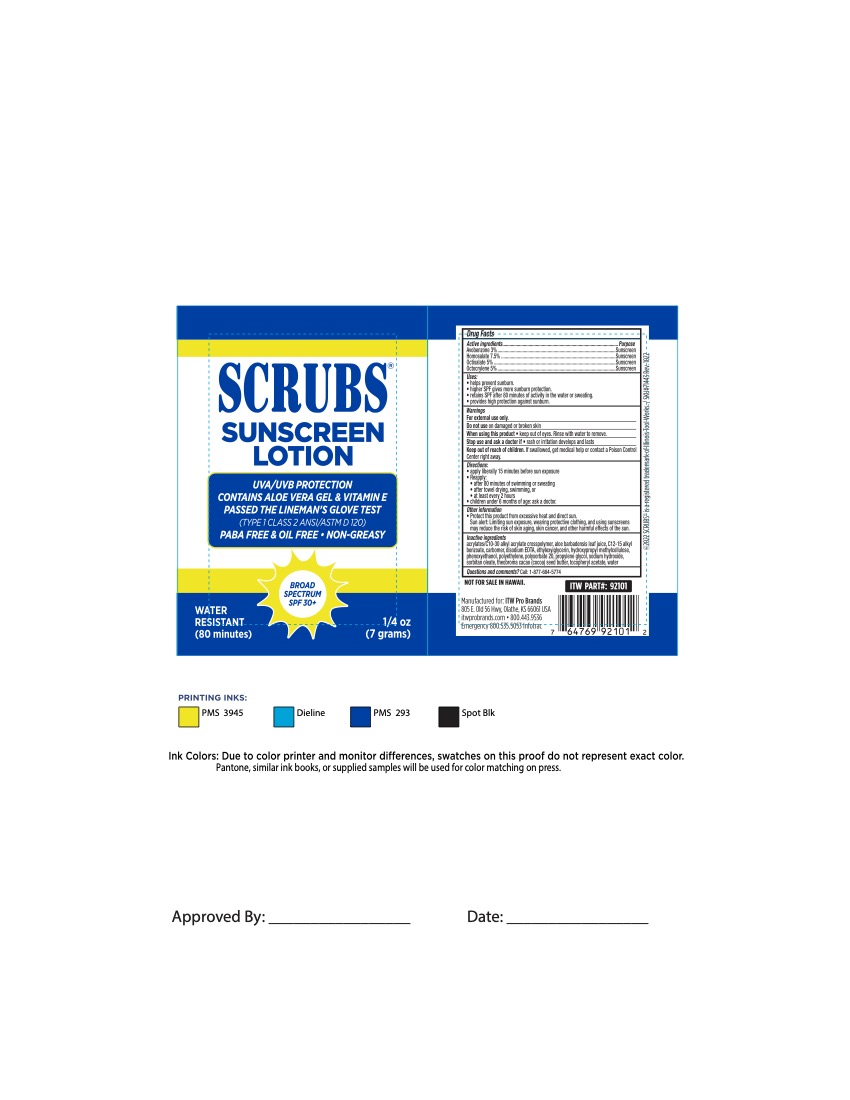 DRUG LABEL: Srubs Sunscreen
NDC: 51239-4921 | Form: LOTION
Manufacturer: ITW Pro Brands
Category: otc | Type: HUMAN OTC DRUG LABEL
Date: 20251205

ACTIVE INGREDIENTS: OCTOCRYLENE 5 g/100 g; AVOBENZONE 3 g/100 g; HOMOSALATE 7 g/100 g; OCTISALATE 5 g/100 g
INACTIVE INGREDIENTS: ALKYL (C12-15) BENZOATE; CARBOMER HOMOPOLYMER, UNSPECIFIED TYPE; DISODIUM EDTA-COPPER; SODIUM HYDROXIDE; PEG-6 SORBITAN OLEATE; THEOBROMA CACAO WHOLE; ETHYLHEXYLGLYCERIN; POLYSORBATE 20; METHYLCELLULOSE, UNSPECIFIED; PROPYLENE GLYCOL PROPYL ETHER; MEDIUM DENSITY POLYETHYLENE; WATER; ALOE VERA LEAF; .ALPHA.-TOCOPHEROL ACETATE; PHENOXYETHANOL; ACRYLATES CROSSPOLYMER-6

Scrubs Sunscreen Lotion 30+
51239-4921-1

Active ingredients

Avobenzone 3%

Homosalate 7.5%

Octisalate 5%

Octocrylene 5%

Purpose

Sunscreen

Sunscreen

Sunscreen

Sunscreen

Uses

- helps prevent sunburn.
- higher SPF gives more sunburn protection.
- retains SPF after 80 minutes of activity in the water or sweating.
- provides high protection against sunburn.

Warnings

For external use only

Do not use

on damaged or broken skin

When using this product

- keep out of the eyes. Rinse with water to remove.

Stop use and ask a doctor if

- rash or irritation develops and lasts

Keep out of the reach of children.

If swallowed, get medical help or contact a Poison Control Center right away.

Directions

- apply liberally 15 minutes before sun exposure
- Reapply:
- after 80 minutes of swimming or sweating
- after towel drying, swimming, or
- at least every 2 hours
- children under 6 months of age: ask a doctor.

Other information

- Protect this product from excessive heat and direct sun.

Sun alert: Limiting sun exposure, wearing protective clothing, and using sunscreens may reduce the risk of skin aging, skin cancer, and other harmful effects of the sun.

Inactive ingredients

acrylates/C10-30 alkyl acrylate crosspolymer, aloe barbadensis leaf juice, C12-15 alkyl benzoate, carbomer, disodium EDTA, ethylhexylglycerin, hydroxypropyl methylcellulose, phenoxyethanol, polyethylene, polysorbate 20, propylene glycol, sodium hydroxide, sorbitan oleate, theobroma cacao (cocoa) seed butter, tocopheryl acetate, water.

Questions and comments?

Call: 1-877-684-5774